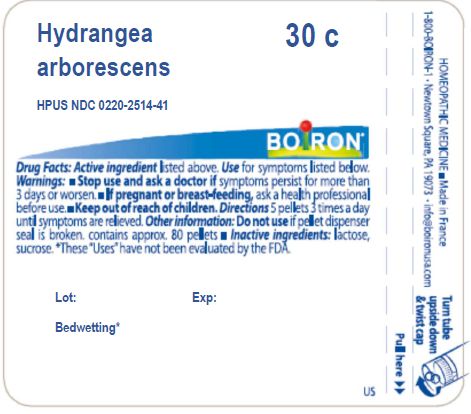 DRUG LABEL: Hydrangea arborescens
NDC: 0220-2514 | Form: PELLET
Manufacturer: Boiron
Category: homeopathic | Type: HUMAN OTC DRUG LABEL
Date: 20231113

ACTIVE INGREDIENTS: HYDRANGEA ARBORESCENS ROOT 30 [hp_C]/30 [hp_C]
INACTIVE INGREDIENTS: SUCROSE; LACTOSE, UNSPECIFIED FORM

Hydrangea arborescens

ACTIVE INGREDIENT

Hydrangea arborescens 30C

INDICATIONS AND USAGE

Bedwetting*

Stop use and ask a doctor if symptoms persist for more than 3 days or worsen

PREGNANCY OR BREAST FEEDING

If pregnant or breast-feeding ask a health professional before use

Keep out of reach of children

DOSAGE AND ADMINISTRATION

5 pellets 3 times a day until symptoms are relieved

Do not use if pellet dispenser seal is broken, contains approx 80 pellets

INACTIVE INGREDIENT

lactose, sucrose

QUESTIONS

1-800-BOIRON-1, Newtown Square, PA 19073-3267, info@boironusa.com

These "Uses" have not been evaluated by the FDA